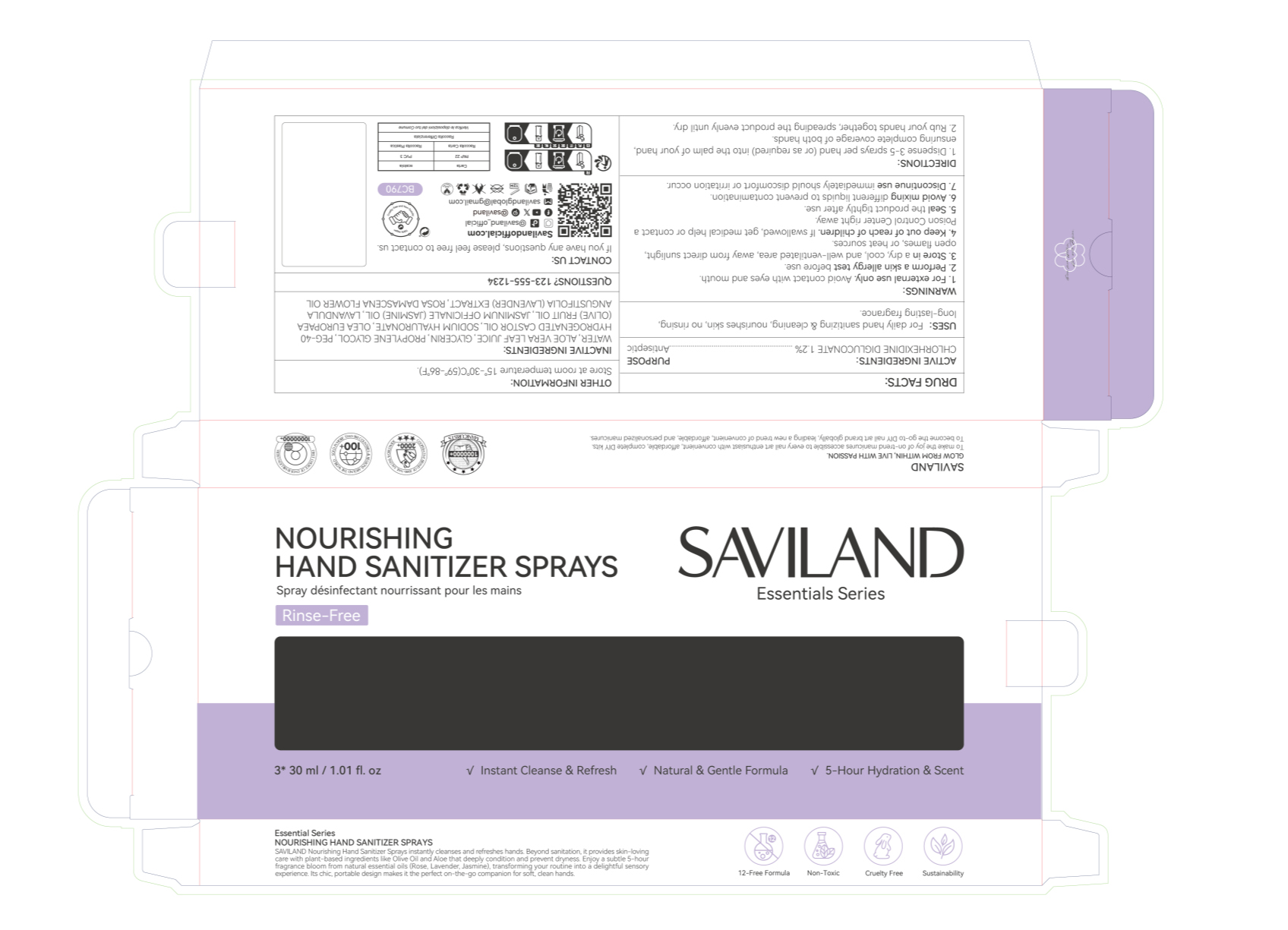 DRUG LABEL: NOURISHING HAND SANITIZER SPRAYS
NDC: 85966-003 | Form: LIQUID
Manufacturer: GUANGZHOU SAWEILAN IMPORT & EXPORT TRADING CO., LTD
Category: otc | Type: HUMAN OTC DRUG LABEL
Date: 20250912

ACTIVE INGREDIENTS: CHLORHEXIDINE DIGLUCONATE 0.012 g/1 mL
INACTIVE INGREDIENTS: WATER; GLYCERIN; SODIUM HYALURONATE; ROSA DAMASCENA FLOWER OIL; JASMINUM OFFICINALE (JASMINE) FLOWER; OLEA EUROPAEA (OLIVE) FRUIT OIL; LAVANDULA ANGUSTIFOLIA FLOWERING TOP; PROPYLENE GLYCOL; PEG-40 HYDROGENATED CASTOR OIL; ALOE VERA LEAF JUICE

85966-003 Nourishing Hand Sanitizer Spray

ACTIVE INGREDIENT

CHLORHEXIDINE DIGLUCONATE 1.2%

PURPOSE

Antiseptic

INDICATIONS AND USAGE

USES: For daily hand sanitizing & ceaning, nourishes skin, no rinsing long-lasting fragrance.

WARNINGS

For external use only. Avoid contact with eyes and mouth

WHEN USING

Perform a skin allergy test before use.

Seal the product tightly after use.

Avoid mixing different liquids to prevent contamination.

Store in a dry, cool, and well-ventilated area, away from direct sunlight,open flames, or heat sources.

Discontinue use immediately should discomfort or irritation occur.

Keep out of reach of children. lf swallowed, get medical help or contact aPoison Control Center right away.

DOSAGE AND ADMINISTRATION

1.Dispense 3-5 sprays per hand (or as required) into the palm of your hand,ensuring complete coverage of both hands.
2. Rub your hands together, spreading the product evenly until dry.

STORAGE AND HANDLING

Store at room temperature 15°-30°C(59°-86°F)

INACTIVE INGREDIENT

WATER
ALOE VERA LEAF JUICE
GLYCERIN
PROPYLENE GLYCOL
PEG-40 HYDROGENATED CASTOR OIL
SODIUM HYALURONATE
OLEA EUROPAEA (OLIVE) FRUIT OIL
JASMINUM OFFICINALE (JASMINE) OIL
LAVANDULA ANGUSTIFOLIA (LAVENDER) EXTRACT
ROSA DAMASCENA FLOWER OIL